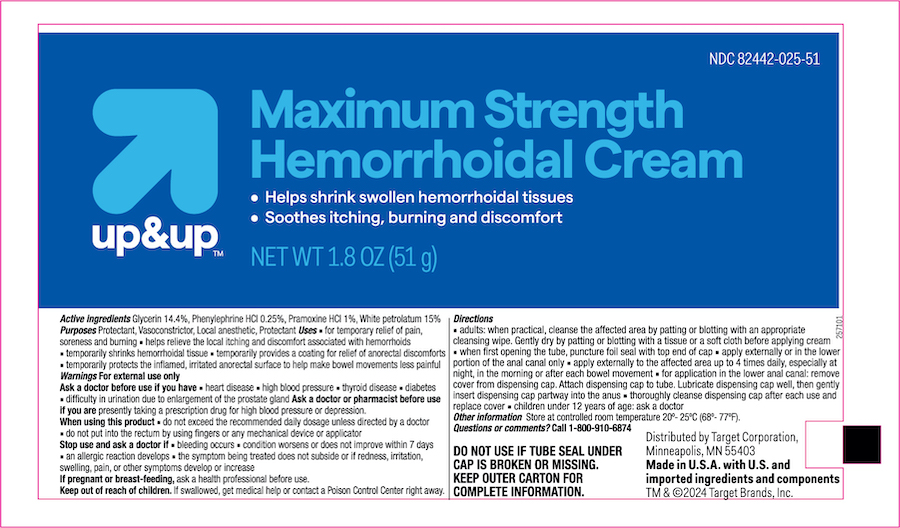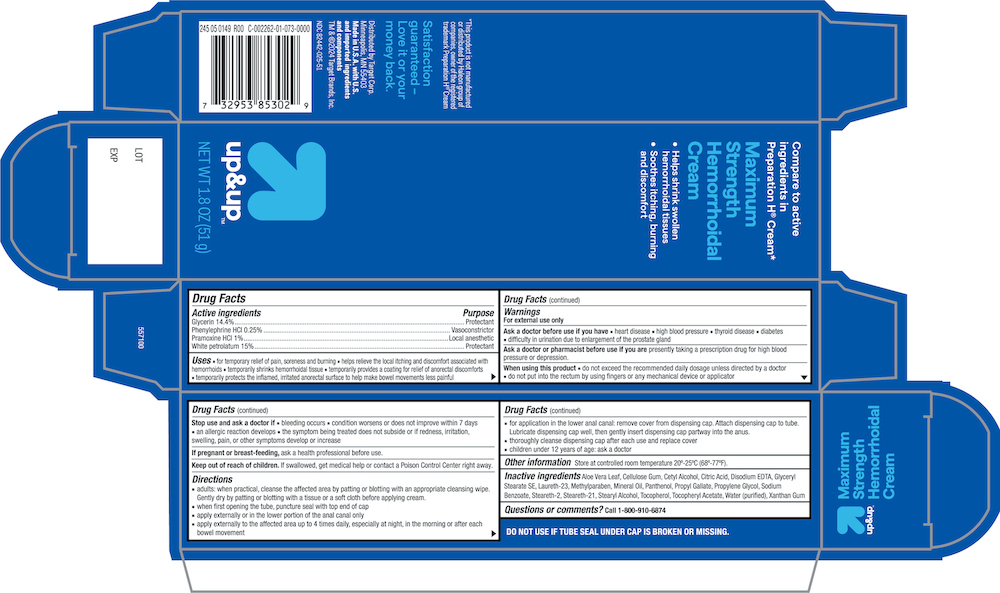 DRUG LABEL: Up and Up Hemorrhoid MAX STRENGTH
NDC: 82442-025 | Form: CREAM
Manufacturer: Target Corporation
Category: otc | Type: HUMAN OTC DRUG LABEL
Date: 20240808

ACTIVE INGREDIENTS: GLYCERIN 144 mg/1 g; PHENYLEPHRINE HYDROCHLORIDE 2.5 mg/1 g; PRAMOXINE HYDROCHLORIDE 10 mg/1 g; PETROLATUM 150 mg/1 g
INACTIVE INGREDIENTS: ALOE VERA LEAF; CARBOXYMETHYLCELLULOSE SODIUM, UNSPECIFIED; CETYL ALCOHOL; CITRIC ACID MONOHYDRATE; EDETATE DISODIUM; GLYCERYL STEARATE SE; METHYLPARABEN; MINERAL OIL; PANTHENOL; PROPYL GALLATE; PROPYLENE GLYCOL; SODIUM BENZOATE; STEARETH-2; STEARETH-21; STEARYL ALCOHOL; TOCOPHEROL; .ALPHA.-TOCOPHEROL ACETATE; WATER; XANTHAN GUM

Active ingredients

Glycerin 14.4%

Phenylephrine HCl 0.25%

Pramoxine 1%

White petrolatum 15%

Purpose

Protectant

Vasoconstrictor

Local anesthetic

Protectant

Uses

- for temporary relief of pain, soreness and burning
- helps relieve the local itching and discomfort associated with hemorrhoids
- temporarily shrinks hemorrhoidal tissue
- temporarily provides a coating for relief of anorectal discomforts
- temporarily protects the inflamed irritated anorectal surface to help make bowel movements less painful

Ask a Doctor before use if you have

- heart disease
- high blood pressure
- thyroid disease
- diabetes
- difficulty in urination due to enlargement of the prostate gland

Ask a doctor or pharmacist before use if you are presently taking a prescription drug for high blood pressure or depression.

When using this product

- do not exceed the recommended daily dosage unless directed by a doctor
- do not put into the rectum by using fingers or any mechanical device or applicator

Stop use and ask a doctor if

bleeding occurs
condition worsens or does not improve within 7 days
an allergic reaction develops
the symptom being treated does not subside or if redness, irritation, swelling, pain, or other symptoms develop or increase

PREGNANCY OR BREAST FEEDING

If pregnant or breast-feeding,ask a health professional before use.

Keep out of reach of children.If swallowed, get medical help or contact a Poison Control Center right away.

Directions

- adults: when practical, cleanse the affected area by patting or blotting with an appropriate cleansing wipe. Gently dry by patting or blotting with a tissue or a soft cloth before applying this cream.
- apply externally to the affected area up to 4 times daily, especially at night, in the morning or after each bowel movement
- children under 12 years of age: ask a doctor

Other information

Store at controlled room temperature 20-25°C (68-77°F)

Inactive ingredients

Aloe Barbadensis Leaf, Cellulose Gum, Cetyl Alcohol, Citric Acid , Citric Acid Anhydrous, Disodium EDTA, Glyceryl Stearate SE, Methylparaben, Mineral Oil, Panthenol, Propyl Gallate, Propylene Glycol, Sodium Benzoate, Steareth-2, Steareth-21, Stearyl Alcohol, Tocopherol, Tocopheryl Acetate, Water (purified), Xanthan Gum

Principal Display Panel

Target up & up NDC 82442-025-51

Maximum Strength

Hemorroidal Cream

NET WT 1.8 OZ (51g)